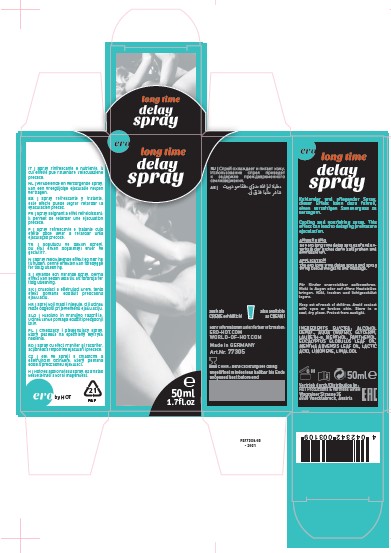 DRUG LABEL: ERO LONG TIME DELAY
NDC: 71326-207 | Form: SPRAY
Manufacturer: HOT PRODUCTIONS AND VERTRIEBS GMBH
Category: homeopathic | Type: HUMAN OTC DRUG LABEL
Date: 20231005

ACTIVE INGREDIENTS: EUCALYPTUS OIL 0.1 g/100 mL
INACTIVE INGREDIENTS: ALCOHOL; WATER; GLYCERIN; POLIDOCANOL; PANTHENOL; LACTIC ACID; LIMONENE, (+)-; LINALOOL, (+)-; MENTHOL; MENTHA ARVENSIS LEAF OIL

HOT PRODUCTS - Ero Long Time Delay Spray (71326-207)

ACTIVE INGREDIENTS

Eucalyptus Globulus Leaf Oil 0.1x HPUS

PURPOSE

Topical Anesthetic

USE

Cooling and nourishing spray. This effect can lead to delaying premature ejaculation.

WARNINGS

Avoid contact with the eyes or broken skin.

Keep out of reach of children.

APPLICATION

The ero long time delay spray and spray thinly below the glans and massage.

OTHER INFORMATION

- Store in a cool, dry place. Protect from sunlight.

INACTIVE INGREDIENTS

ALCOHOL DENAT., AQUA (WATER), GLYCERIN, LAURETH-9, MENTHOL, PANTHENOL, EUCALYPTUS GLOBULUS LEAF OIL,
MENTHA ARVENSIS LEAF OIL, LACTIC ACID, LIMONENE, LINALOOL